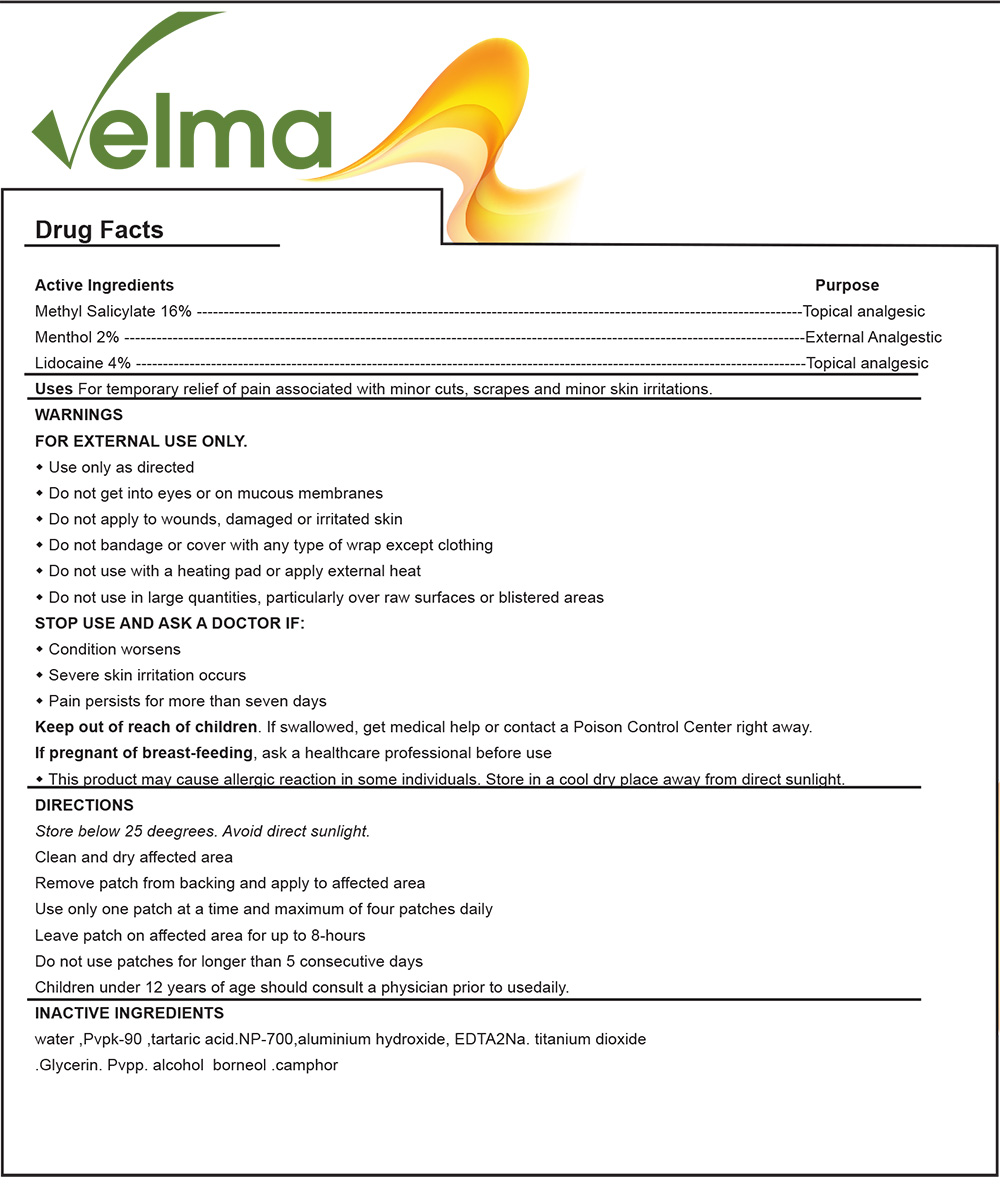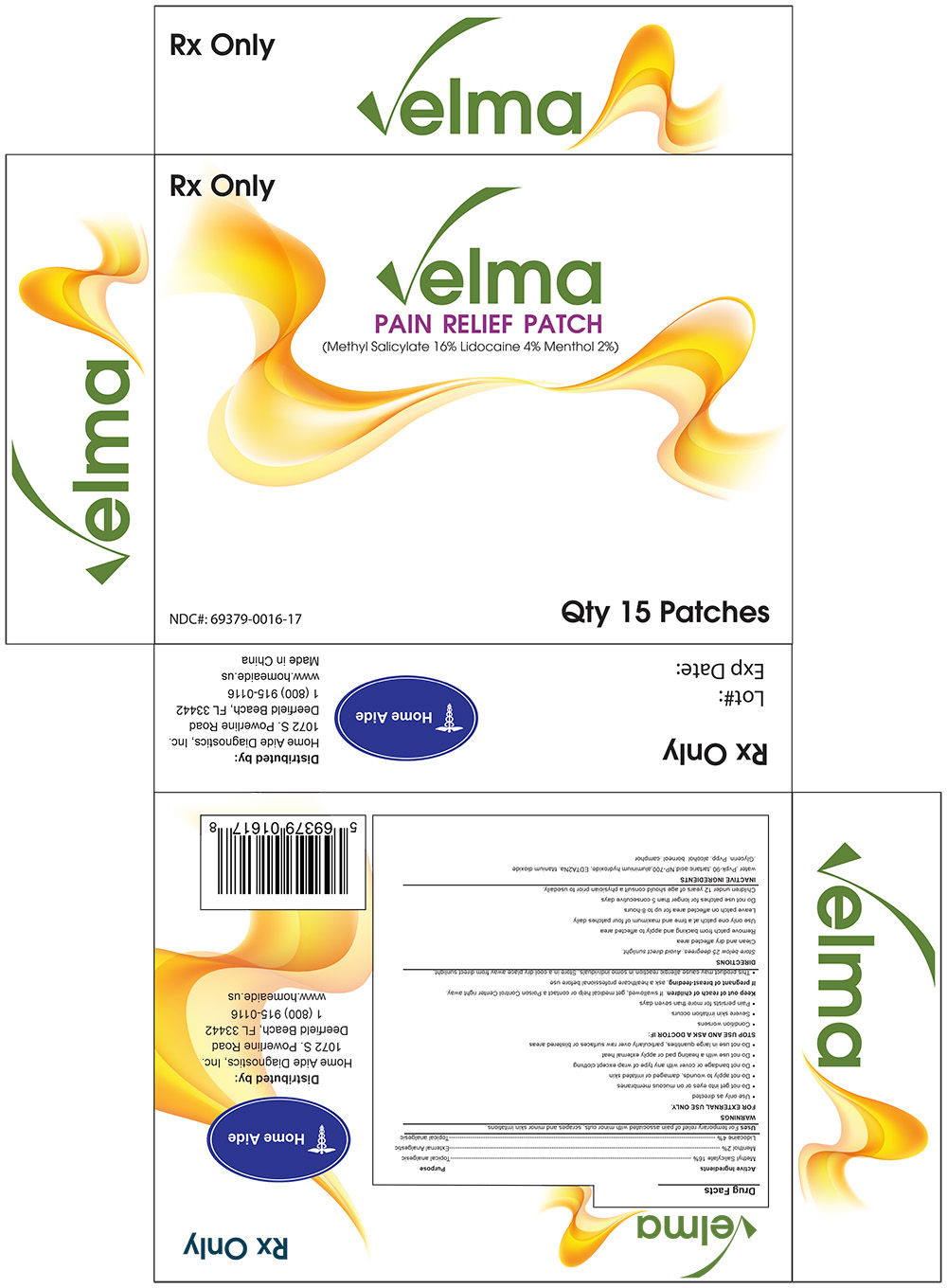 DRUG LABEL: Velma Pain Relief Patch
NDC: 69379-016 | Form: PATCH
Manufacturer: Home Aide Diagnostics, Inc.
Category: prescription | Type: HUMAN PRESCRIPTION DRUG LABEL
Date: 20141202

ACTIVE INGREDIENTS: LIDOCAINE 4 g/100 g; MENTHOL 2 g/100 g; Methyl Salicylate 16 g/100 g

VELMA PAIN RELIEF PATCH

GENERAL PRECAUTIONS

This product may cause allergic reactions in some individuals.